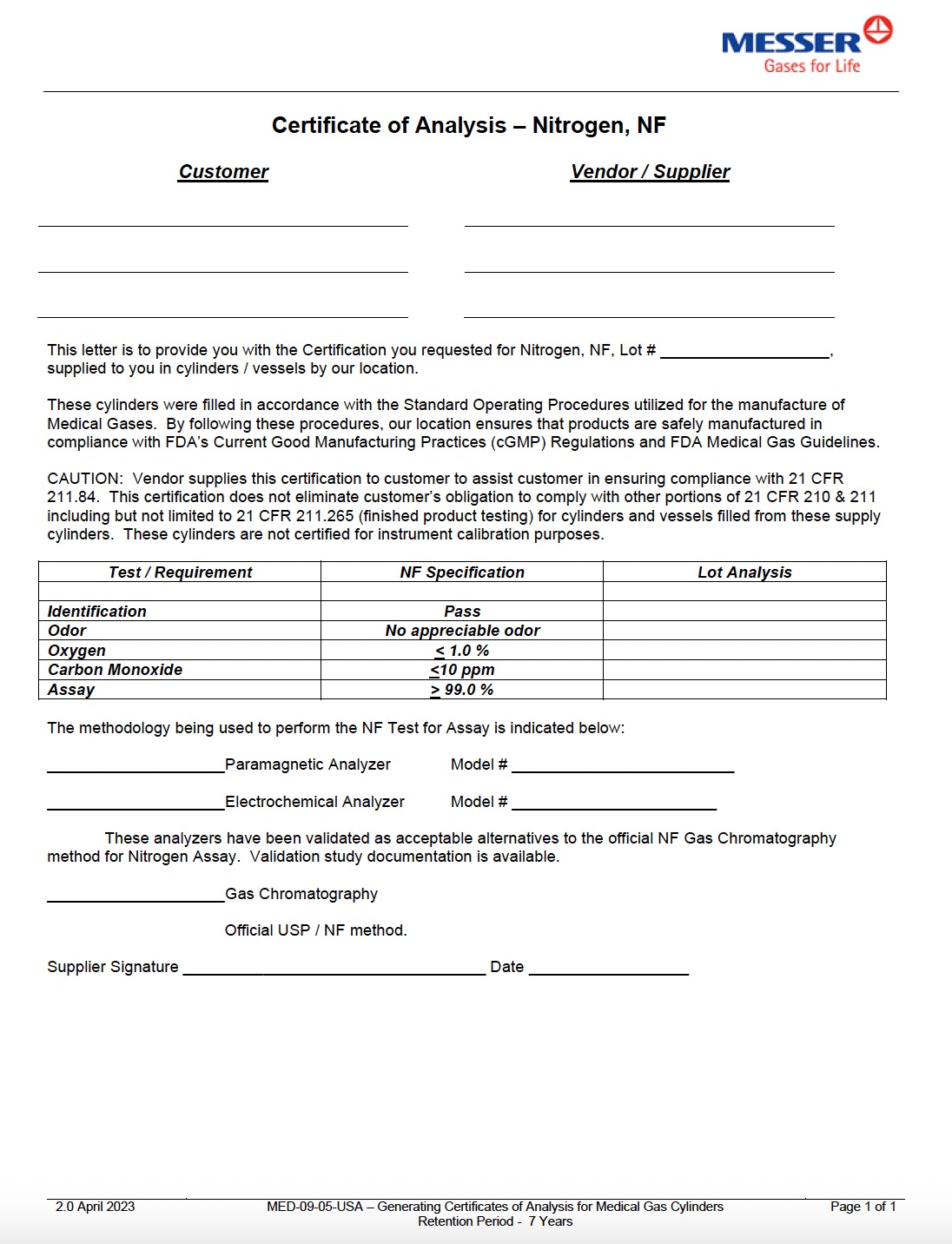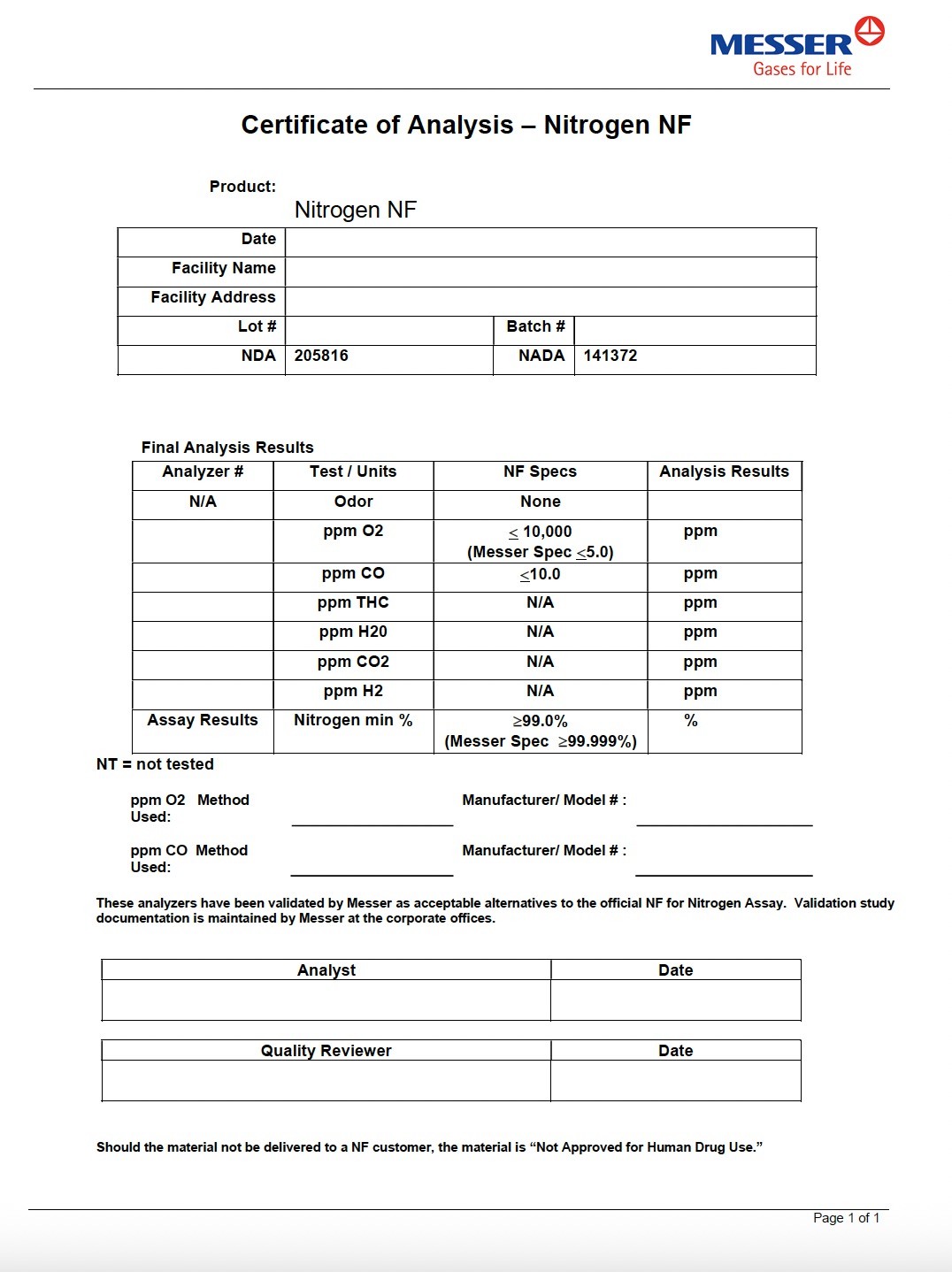 DRUG LABEL: Nitrogen
NDC: 52374-016 | Form: GAS
Manufacturer: Messer Gas Puerto Rico, Inc
Category: prescription | Type: HUMAN PRESCRIPTION DRUG LABEL
Date: 20251118

ACTIVE INGREDIENTS: NITROGEN 995 mL/1 L

Messer PR - Nitrogen NF Bulk Liquid -016

PACKAGE LABEL

Certificate of Analysis – Nitrogen, NF

Customer Vendor / Supplier
This letter is to provide you with the Certification you requested for Nitrogen, NF, Lot #.
supplied to you in cylinders / vessels by our location.

These cylinders were filled in accordance with the Standard Operating Procedures utilized for the manufacture of
Medical Gases. By following these procedures, our location ensures that products are safely manufactured in
compliance with FDA’s Current Good Manufacturing Practices (cGMP) Regulations and FDA Medical Gas Guidelines.

CAUTION: Vendor supplies this certification to customer to assist customer in ensuring compliance with 21 CFR
211.84. This certification does not eliminate customer’s obligation to comply with other portions of 21 CFR 210 & 211
including but not limited to 21 CFR 211.265 (finished product testing) for cylinders and vessels filled from these supply
cylinders. These cylinders are not certified for instrument calibration purposes.

Test / Requirement

NF Specification

Lot Analysis

Identification

Pass

Odor

No appreciable odor

Oxygen

< 1.0 %

Carbon Monoxide

≤10 ppm

Assay

≥ 99.0 %

The methodology being used to perform the NF Test for Assay is indicated below:

Paramagnetic Analyzer Model #

Electrochemical Analyzer Model #

These analyzers have been validated as acceptable alternatives to the official NF Gas Chromatography
method for Nitrogen Assay. Validation study documentation is available.

Gas Chromatography

Official USP / NF method.

Supplier Signature Date

PACKAGE LABEL

Certificate of Analysis – Nitrogen NF

Product:
Nitrogen NF

Date

Facility Name

Facility Address

Lot #

NDA

205816

Batch #

NADA 141372

Final Analysis Results

Analyzer #

Test / Units

NF Specs

Analysis Results

N/A

Odor

None

ppm O₂

≤ 10,000

ppm

(Messer Spec ≤5.0)

ppm CO

≤10.0

ppm

ppm THC

N/A

ppm

ppm H₂O

N/A

ppm

ppm CO₂

N/A

ppm

ppm H₂

N/A

ppm

Assay Results

Nitrogen min %

≥99.0%

%

(Messer Spec ≥99.999%)

NT = not tested

ppm O₂ Method Used: Manufacturer / Model #:

ppm CO Method Used: Manufacturer / Model #:

These analyzers have been validated by Messer as acceptable alternatives to the official NF for Nitrogen Assay.
Validation study documentation is maintained by Messer at the corporate offices.

Analyst

Date

Quality Reviewer

Date

Should the material not be delivered to a NF customer, the material is “Not Approved for Human Drug Use.”